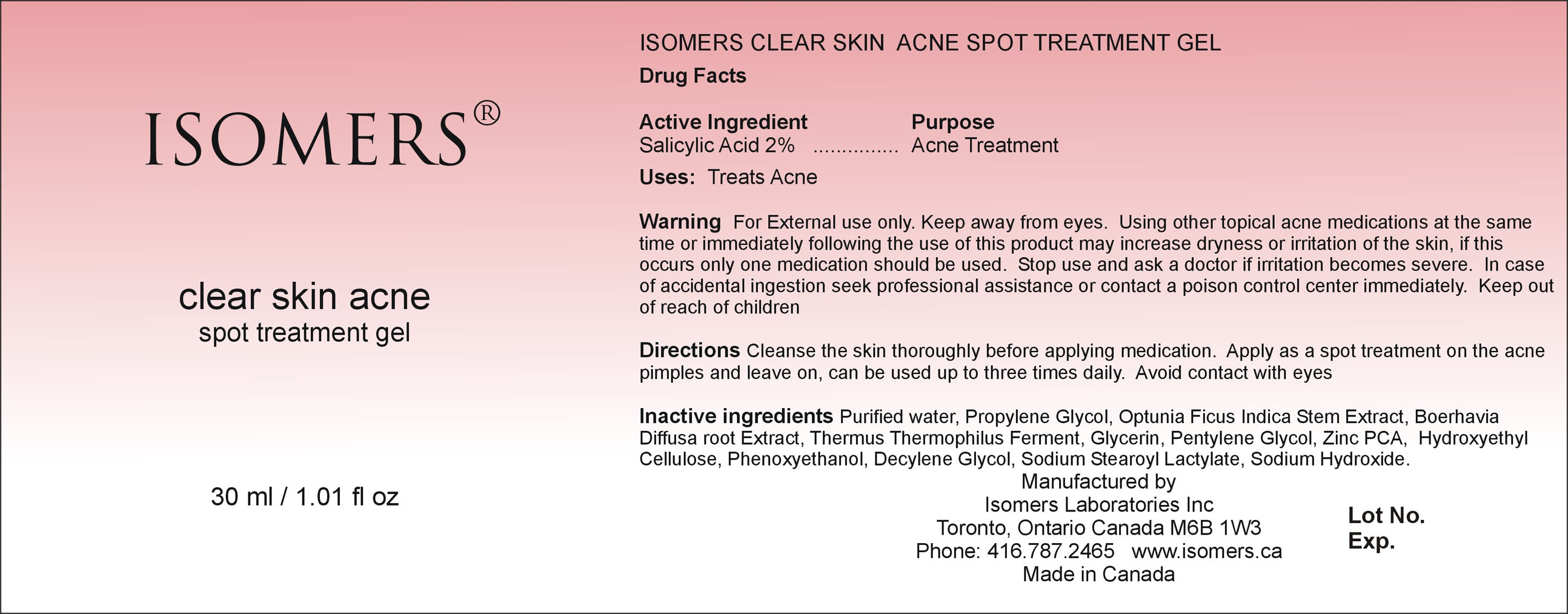 DRUG LABEL: Isomers Clear Skin Acne Spot Treatment 
NDC: 64990-601 | Form: GEL
Manufacturer: Isomers Laboratories Inc
Category: otc | Type: HUMAN OTC DRUG LABEL
Date: 20100301

ACTIVE INGREDIENTS: SALICYLIC ACID 0.02 mL/1 mL
INACTIVE INGREDIENTS: WATER; PROPYLENE GLYCOL; OPUNTIA FICUS-INDICA; GLYCERIN; HYDROXYETHYL CELLULOSE (2000 CPS AT 1%); PHENOXYETHANOL; SODIUM HYDROXIDE

DRUG FACTS

ACTIVE INGREDIENT

Enter section text here

Active Ingredient:

Salicylic Acid 2%

PURPOSE

Enter section text here

Purpose:

Acne Treatment

ASK DOCTOR

Enter section text here

Stop use and ask doctor

If irritation becomes severe

KEEP OUT OF REACH OF CHILDREN

Enter section text here

Keep out of reach of children

WARNINGS

Enter section text here

Warnings :

- For external use only
- Keep away from eyes
- Using other topical acne medications at the same time or immediately following the use of this product may increase dryness or irritation of the skin, if this occurs only one medication should be used.
- In case of accidental ingestion seek professional assistance or contact a poison control center immediately

INACTIVE INGREDIENT

Enter section text here

Inactive Ingredients :

Purified Water, Propylene Glycol, Optunia Ficus Indica Stem Extract, Boerhavia Diffusa root Extract, Thermus Thermophilus Ferment, Glycerin, Pentylene Glycol, Zinc PCA, Hydroxyethyl Cellulose, Phenoxyethanol, Decylene Glycol, Sodium Stearoyl Lacylate, Sodium Hydroxide.

PACKAGE LABEL

CSAST30.jpg